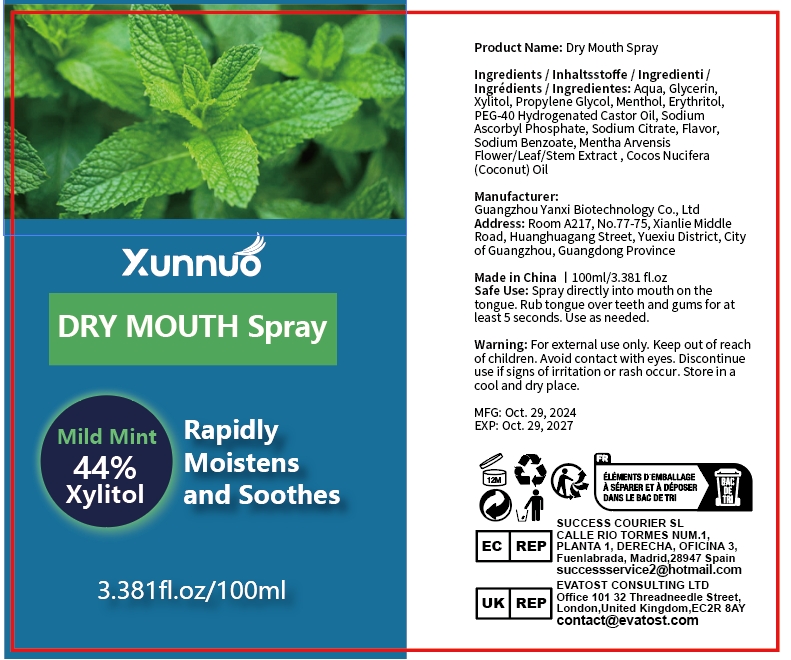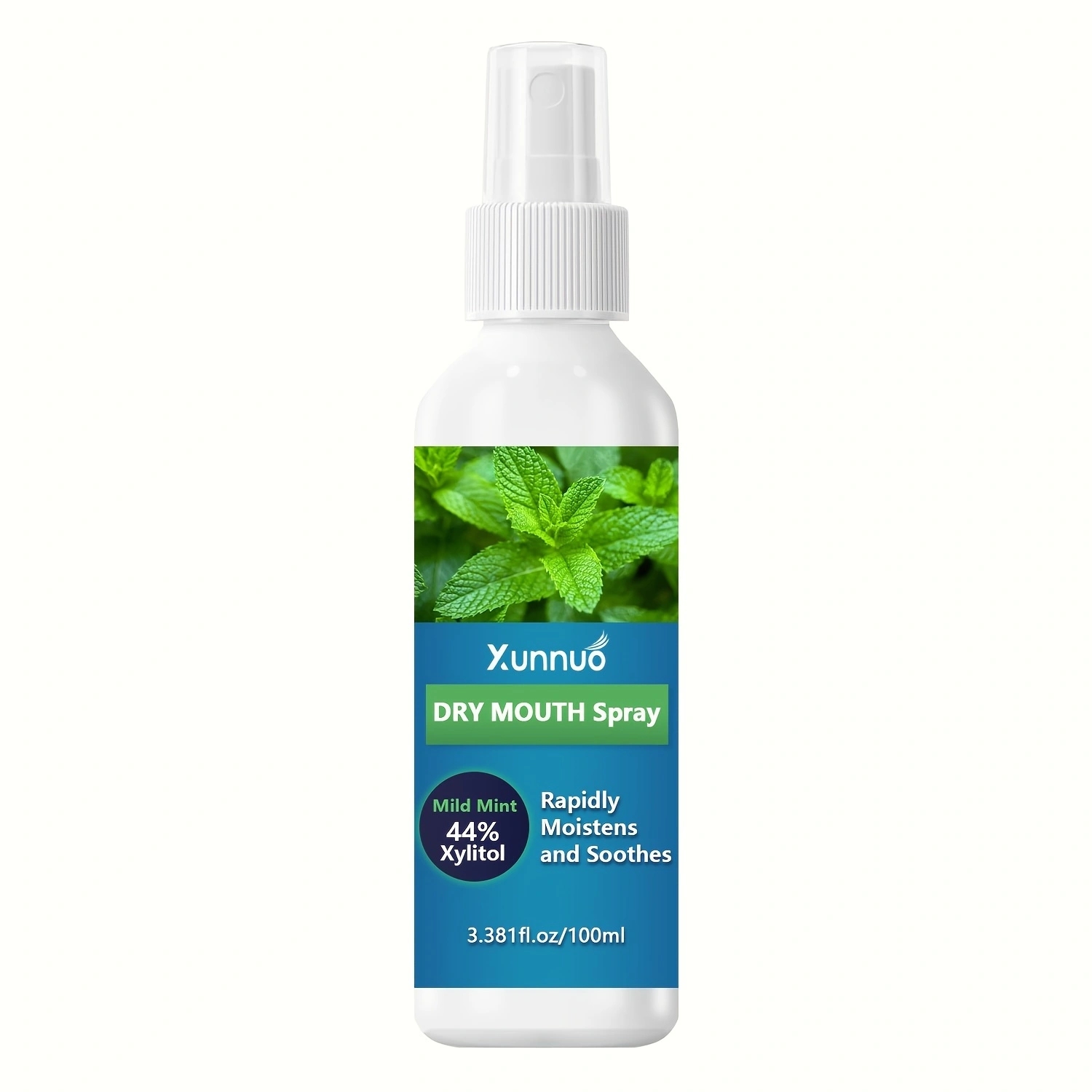 DRUG LABEL: Peppermint mouthspray
NDC: 84025-257 | Form: SPRAY
Manufacturer: Guangzhou Yanxi Biotechnology Co., Ltd
Category: otc | Type: HUMAN OTC DRUG LABEL
Date: 20241110

ACTIVE INGREDIENTS: GLYCERIN 5 mg/100 mL; XYLITOL 3 mg/100 mL
INACTIVE INGREDIENTS: WATER

DOSAGE AND ADMINISTRATION

Spray directly into mouth on the tongue. Rub tongue over teeth and gums for at least 5 seconds.Use as needed.

WARNINGS

keep out of children

INACTIVE INGREDIENT

Aqua

INDICATIONS AND USAGE

This essential peppermint oil spray is a must-have for your daily regimen.

Keep out of children

PURPOSE

Keep your breath fresh.